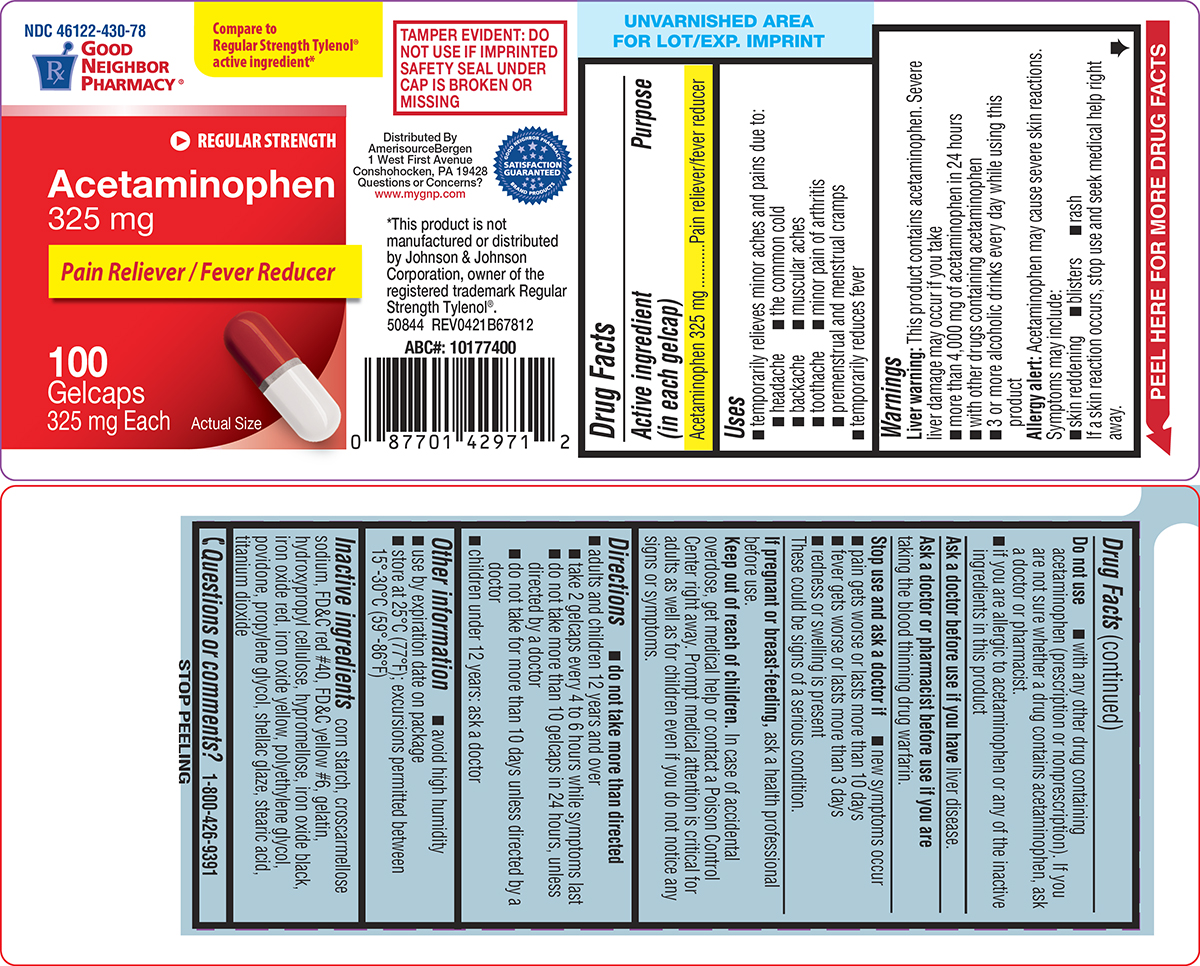 DRUG LABEL: Acetaminophen
NDC: 46122-430 | Form: TABLET, COATED
Manufacturer: Amerisource Bergen
Category: otc | Type: HUMAN OTC DRUG LABEL
Date: 20250324

ACTIVE INGREDIENTS: ACETAMINOPHEN 325 mg/1 1
INACTIVE INGREDIENTS: STARCH, CORN; CROSCARMELLOSE SODIUM; FD&C RED NO. 40; FD&C YELLOW NO. 6; GELATIN, UNSPECIFIED; HYDROXYPROPYL CELLULOSE, UNSPECIFIED; HYPROMELLOSE, UNSPECIFIED; FERROSOFERRIC OXIDE; FERRIC OXIDE RED; FERRIC OXIDE YELLOW; POLYETHYLENE GLYCOL, UNSPECIFIED; POVIDONE, UNSPECIFIED; PROPYLENE GLYCOL; SHELLAC; STEARIC ACID; TITANIUM DIOXIDE

Good Neighbor Pharmacy 44-678

Active ingredient (in each gelcap)

Acetaminophen 325 mg

Purpose

Pain reliever/fever reducer

Uses

- temporarily relieves minor aches and pains due to:
  - headache
  - the common cold
  - backache
  - muscular aches
  - toothache
  - minor pain of arthritis
  - premenstrual and menstrual cramps
- temporarily reduces fever

Warnings

Liver warning: This product contains acetaminophen. Severe liver damage may occur if you take

- more than 4,000 mg of acetaminophen in 24 hours
- with other drugs containing acetaminophen
- 3 or more alcoholic drinks every day while using this product

Allergy alert: Acetaminophen may cause severe skin reactions. Symptoms may include:

- skin reddening
- blisters
- rash

If a skin reaction occurs, stop use and seek medical help right away.

Do not use

- with any other drug containing acetaminophen (prescription or nonprescription). If you are not sure whether a drug contains acetaminophen, ask a doctor or pharmacist.
- if you are allergic to acetaminophen or any of the inactive ingredients in this product

Ask a doctor before use if you have

liver disease.

Ask a doctor or pharmacist before use if you are

taking the blood thinning drug warfarin.

Stop use and ask a doctor if

- new symptoms occur
- pain gets worse or lasts more than 10 days
- fever gets worse or lasts more than 3 days
- redness or swelling is present

These could be signs of a serious condition.

If pregnant or breast-feeding,

ask a health professional before use.

Keep out of reach of children.

In case of accidental overdose, get medical help or contact a Poison Control Center right away. Prompt medical attention is critical for adults as well as for children even if you do not notice any signs or symptoms.

Directions

- do not take more than directed
- adults and children 12 years and over
  - take 2 gelcaps every 4 to 6 hours while symptoms last
  - do not take more than 10 gelcaps in 24 hours, unless directed by a doctor
  - do not take for more than 10 days unless directed by a doctor
- children under 12 years: ask a doctor

Other information

- avoid high humidity
- use by expiration date on package
- store at 25°C (77°F); excursions permitted between 15°-30°C (59°-86°F)

Inactive ingredients

corn starch, croscarmellose sodium, FD&C red #40, FD&C yellow #6, gelatin, hydroxypropyl cellulose, hypromellose, iron oxide black, iron oxide red, iron oxide yellow, polyethylene glycol, povidone, propylene glycol, shellac glaze, stearic acid, titanium dioxide

Questions or comments?

1-800-426-9391

Principal Display Panel

NDC 46122-430-78

Good
Neighbor
Pharmacy®

Compare to
Regular Strength Tylenol®
active ingredient*

REGULAR STRENGTH

Acetaminophen
325 mg

Pain Reliever / Fever Reducer

100
Gelcaps
325 mg Each

Actual Size

TAMPER EVIDENT: DO
NOT USE IF IMPRINTED
SAFETY SEAL UNDER
CAP IS BROKEN OR
MISSING

Distributed By
AmerisourceBergen
1 West First Avenue
Conshohocken, PA 19428
Questions or Concerns?
www.mygnp.com

Good Neighbor Pharmacy Brand Products
Satisfaction Guaranteed

*This product is not
manufactured or distributed
by Johnson & Johnson
Corporation, owner of the
registered trademark Regular
Strength Tylenol®.
50844 REV0421B67812

Good Neighbor 44-678